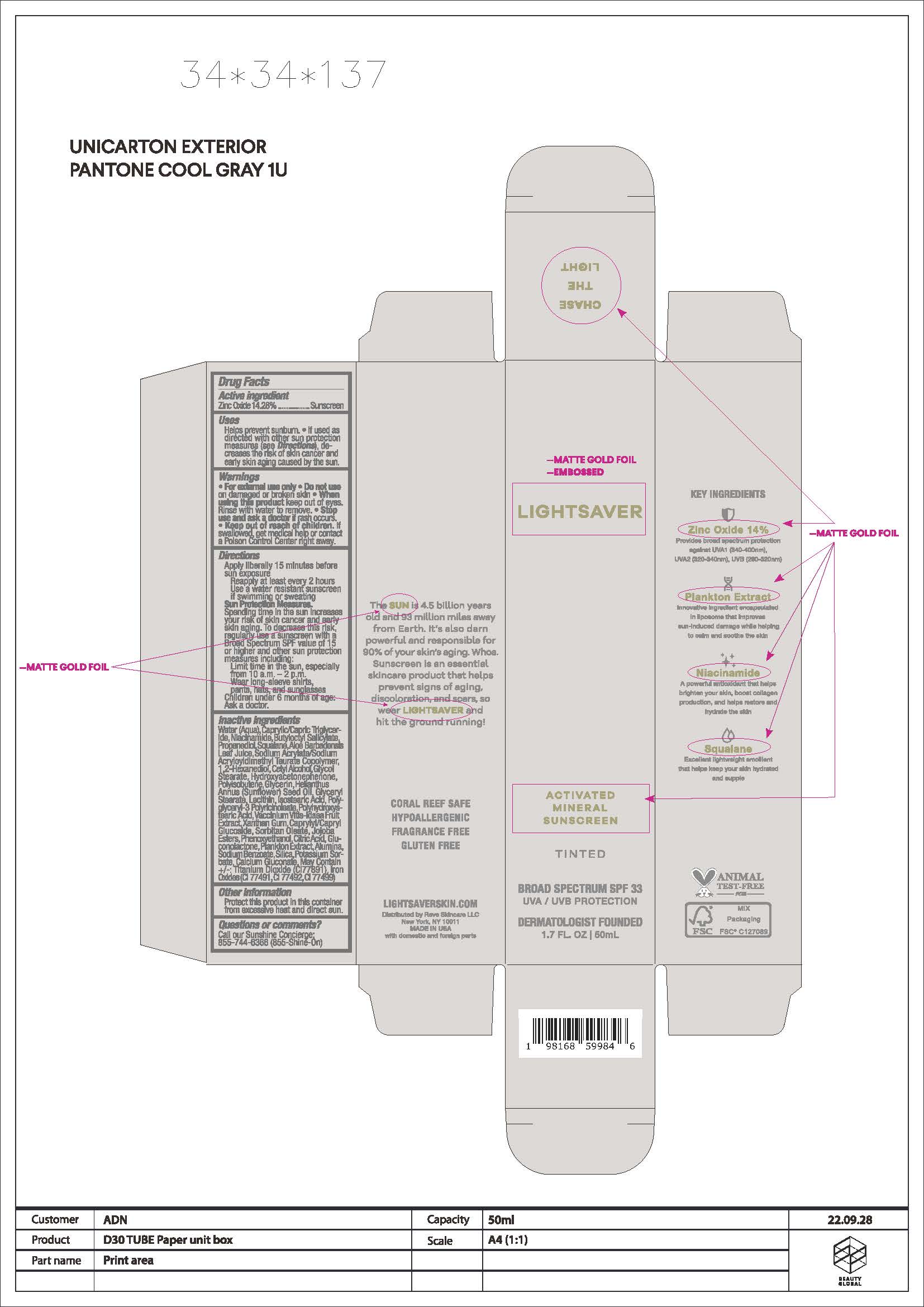 DRUG LABEL: Activated Mineral Sunscreen Tinted
NDC: 83083-002 | Form: CREAM
Manufacturer: Reve Skincare LLC
Category: otc | Type: HUMAN OTC DRUG LABEL
Date: 20251204

ACTIVE INGREDIENTS: ZINC OXIDE 142.8 mg/1 mL
INACTIVE INGREDIENTS: WATER; NIACINAMIDE; BUTYLOCTYL SALICYLATE; PROPANEDIOL; SQUALANE; ALOE VERA LEAF; 1,2-HEXANEDIOL; SODIUM ACRYLATE/SODIUM ACRYLOYLDIMETHYLTAURATE COPOLYMER (4000000 MW); CETYL ALCOHOL; GLYCOL STEARATE; HYDROXYACETOPHENONE; GLYCERIN; HELIANTHUS ANNUUS WHOLE; GLYCERYL STEARATE SE; LECITHIN, SOYBEAN; ISOSTEARIC ACID; POLYGLYCERYL-3 PENTARICINOLEATE; POLYHYDROXYSTEARIC ACID (2300 MW); VACCINIUM VITIS-IDAEA FRUIT OIL; ISOHEXADECANE; XANTHAN GUM; POLYSORBATE 80; PEG-6 SORBITAN OLEATE; PHENOXYETHANOL; JOJOBA OIL; CITRIC ACID ACETATE; GLUCONOLACTONE; ALUMINUM; SODIUM BENZOATE; POTASSIUM SORBATE; SILICON; CALCIUM GLUCONATE; TITANIUM DIOXIDE; BROWN IRON OXIDE

Active Ingredients

Zinc Oxide 14.2%

Uses

• helps prevent sunburn • if used as directed with other
sun protection measures (see Directions), decreases the
risk of skin cancer and early skin aging caused by the sun

Warnings

For external use only
Do not use on damaged or broken skin.
When using this product keep out of eyes. Rinse with water to remove.
Stop use and ask a docor if rash occurs
Keep out of reach of children. If swalled, get medical help or contact a Poison Control Center right away.

Directions

• apply generously 15 minutes before sun exposure
• reapply: •at least every 2 hours.

• use a water resistant sunscreen if swimming or sweating
• Sun Protection Measures. Spending time in the sun

increases your risk of skin cancer and early skin aging. To decrease
this risk, regularly use a sunscreen with a Broad Spectrum SPF
value of 15 or higher and other sun protection measures including:
• limit time in the sun, especially from 10 a.m. - 2 p.m.
• wear long-sleeved shirts, pants, hats, and sunglasses
• children under 6 months of age: Ask a doctor

Inactive ingredients

Water, Caprylic/Capric Triglyceride, Niacinamide, Butyloctyl Salicylate, Propanediol, Squalene, Aloe Barbadensis Leaf Juice, Sodium Acrylate/Sodium Acyloyldimethyl Tauarate Copolymer, 1,2-Hexanediol, Cetyl Alcohol, Glycol Stearate, Helianthus Annuus (Sunflower) Seed Oil, Hydroxyacetophenone, Polyisobutene, Glycerin, Glyceryl Stearate, Lecithin, Isostearic Acid, Polyglyceryl-3 Polyricinoleate, Polyhydroxystearic Acid, Vaccinium Vitis-Idaea Fruit Extract, Xanthan Gum, Caprylyl/Capryl Glucoside, Sorbitan Oleate, Phenoxyethanol, Jojoba Esters, Citric Acid, Gluconolactone, Plankotn Extract, Alumina, Sodium Benzoate, Potassium Sorbate, Silica, Calcium Glucate. May Contain (+/-): Titanium Dioxide (CI77891), Iron Oxides (CI 774941, 77492, 77499)

Other Information

• protect the product in this container from excessive
heat and direct sun

Questions or Comments?

Call our Sunshine Concierge: 855-744-6366 (855-Shine-On)

Purpose

Sunscreen

Keep out of reach of children.

Topical